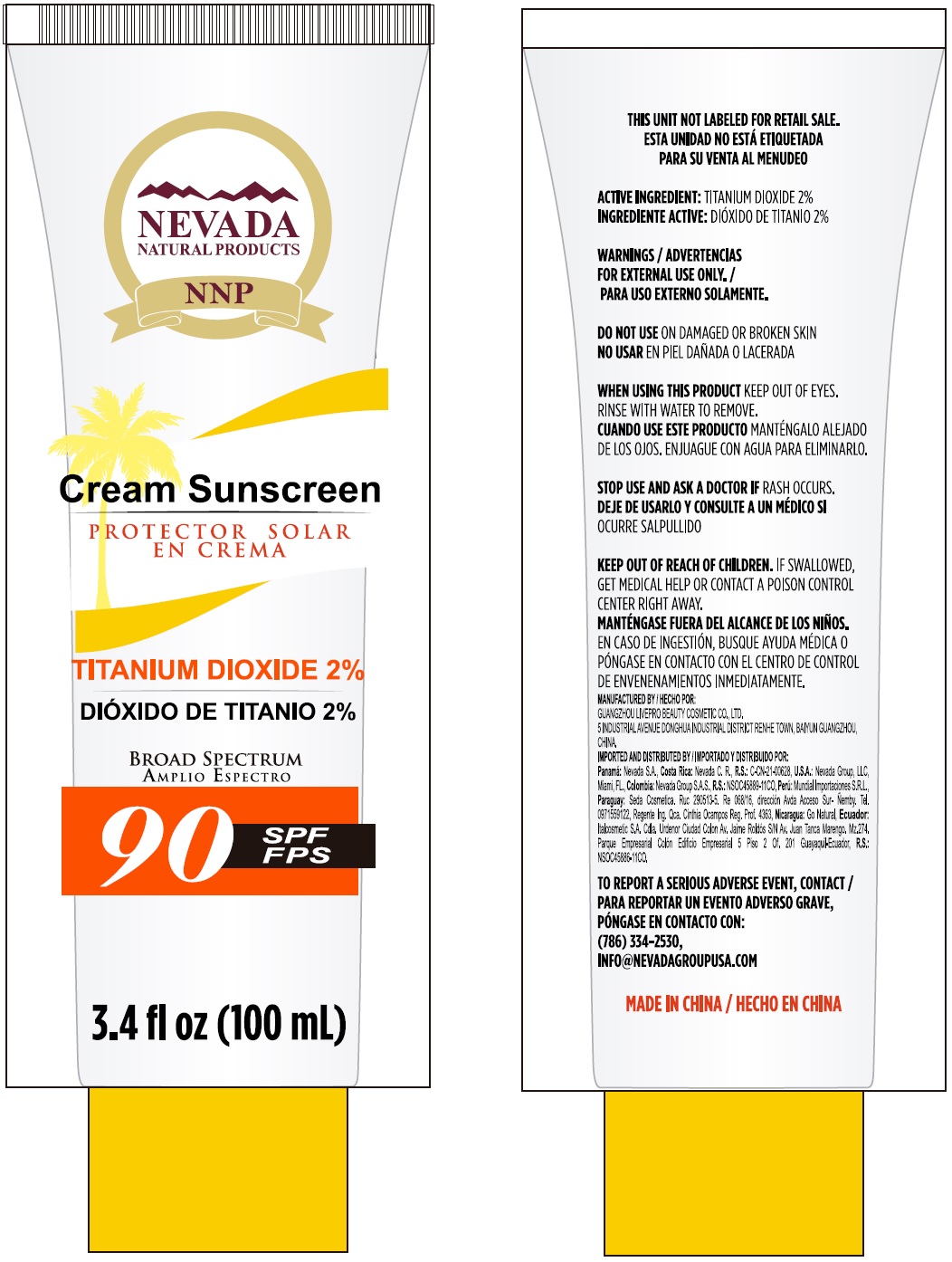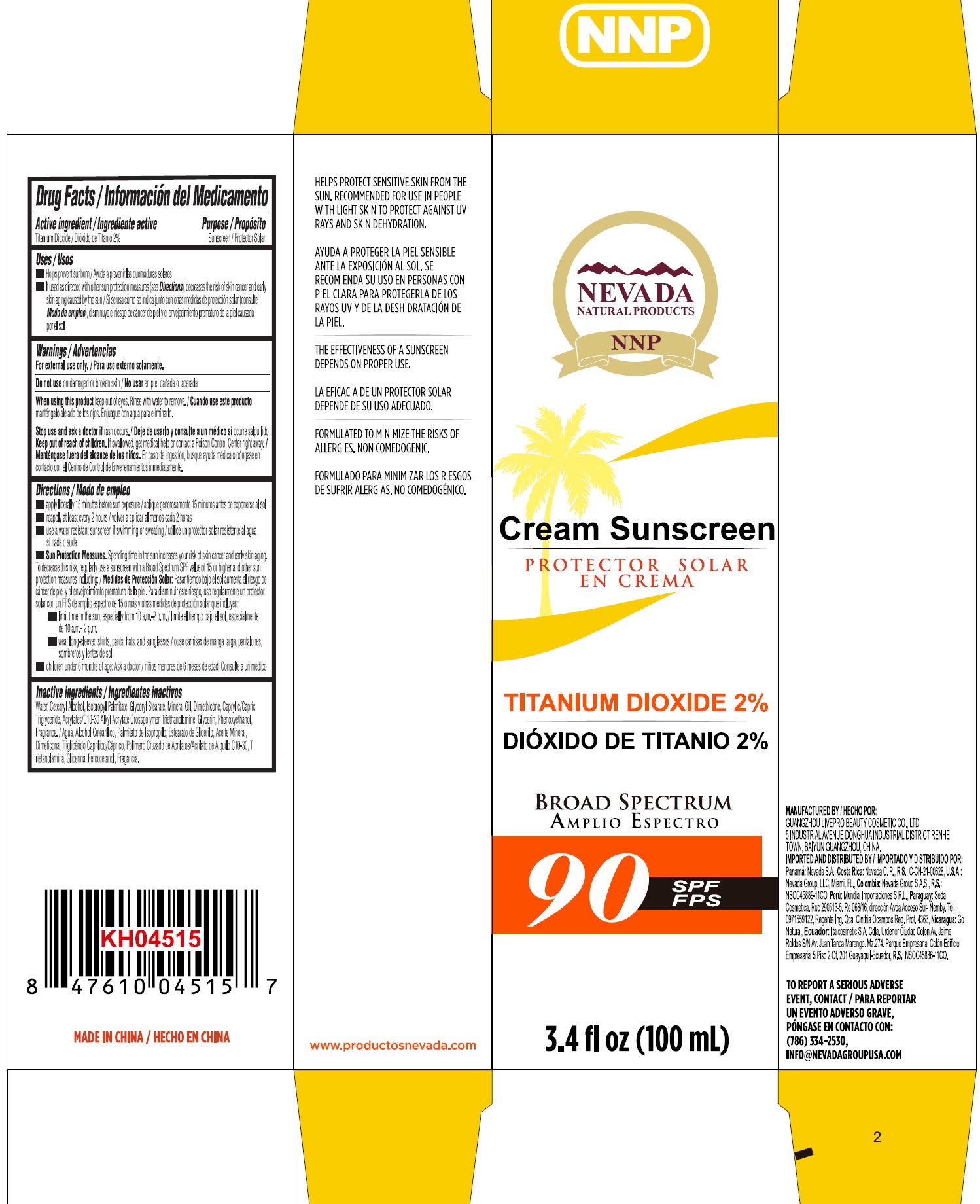 DRUG LABEL: Nevada Natural Products Cream Sunscreen SPF 90
NDC: 82523-001 | Form: CREAM
Manufacturer: Nevada Group L Corp
Category: otc | Type: HUMAN OTC DRUG LABEL
Date: 20220228

ACTIVE INGREDIENTS: TITANIUM DIOXIDE 20 mg/1 mL
INACTIVE INGREDIENTS: CARBOMER INTERPOLYMER TYPE A (55000 CPS); MEDIUM-CHAIN TRIGLYCERIDES; WATER; CETOSTEARYL ALCOHOL; ISOPROPYL PALMITATE; GLYCERYL MONOSTEARATE; MINERAL OIL; DIMETHICONE; TROLAMINE; GLYCERIN; PHENOXYETHANOL

Nevada Natural Products Cream Sunscreen SPF 90

Active ingredient

Titanium Dioxide 2%

Purpose

Sunscreen

Uses

- Helps prevent sunburn
- If used as directed with other sun protection measures (see Directions), decreases the risk of skin cancer and early skin aging caused by the sun

Warnings

For external use only.

Do not use

on damaged or broken skin

When using this product

keep out of eyes. Rinse with water to remove.

Stop use and ask a doctor if

rash occurs.

Keep out of reach of children.

If swallowed, get medical help or contact a Poison Control Center right away.

Directions

- apply liberally 15 minutes before sun exposure
- reapply at least every 2 hours
- use a water resistant sunscreen if swimming or sweating
- Sun Protection Measures. Spending time in the sun increases your risk of skin cancer and early skin aging. To decrease this risk, regularly use a suscreen with a Broad Spectrum SPF value of 15 or higher and other sun protection measures including:
- limit time in the sun, especially from 10 a.m.-2 p.m.
- wear long-sleeved shirts, pants, hats, and sunglasses
- children under 6 months of age: Ask a doctor

Inactive ingredients

Water, Cetearyl Alcohol, Isopropyl Palmitate, Glyceryl Stearate, Mineral Oil, Dimethicone, Caprylic/Capric Triglyceride, Acrylates/C10-30 Alkyl Acrylate Crosspolymer, Triethanolamine, Glycerin, Phenoxyethanol, Fragrance.